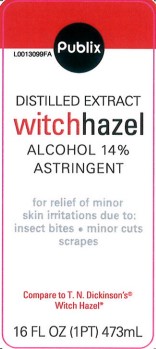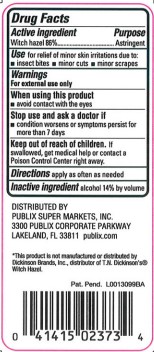 DRUG LABEL: Witch Hazel
NDC: 56062-822 | Form: LIQUID
Manufacturer: Publix Super Markets, Inc.
Category: otc | Type: HUMAN OTC DRUG LABEL
Date: 20260205

ACTIVE INGREDIENTS: WITCH HAZEL 860 mg/1 mL
INACTIVE INGREDIENTS: ALCOHOL

Publix 822.001/822AA
Witch Hazel

Active ingredient

Witch Hazel 86%

Purpose

Astringent

Use

for relief of minor skin irritations due to:

- insects bites
- minor cuts
- monor scrapes

Warnings

For external use only

When using this product

- avoid contact with the eyes

Stop use and ask a doctor if

- condition worses or symptoms last for more than 7 days

Keep out of reach of children.

If swallowed, get medical help or contact a Poison Control Center right away.

Directions

apply as often as needed

Inactive ingredient

alcohol 14% by volume

ADVERSE REACTION

Distributed by Publix Supermarkets, Inc.

3300 Publix Corporate Parkway

Lakeland, FL 33811 publix.com

Disclaimer

*This product is not manufactured or distributed by Dickinson Brands, Inc., distributor of T.N. Dickinson'sWitch Hazel.

principal display panel

Publix

Distilled Extract

Witch Hazel

Alcohol 14%

Astringent

for relief of minor skin irritations due to: insect bites, minor cuts, scrapes

Compare to TN Dickinson's®Witch Hazel*

16 FL OZ (1 PT) 473 mL